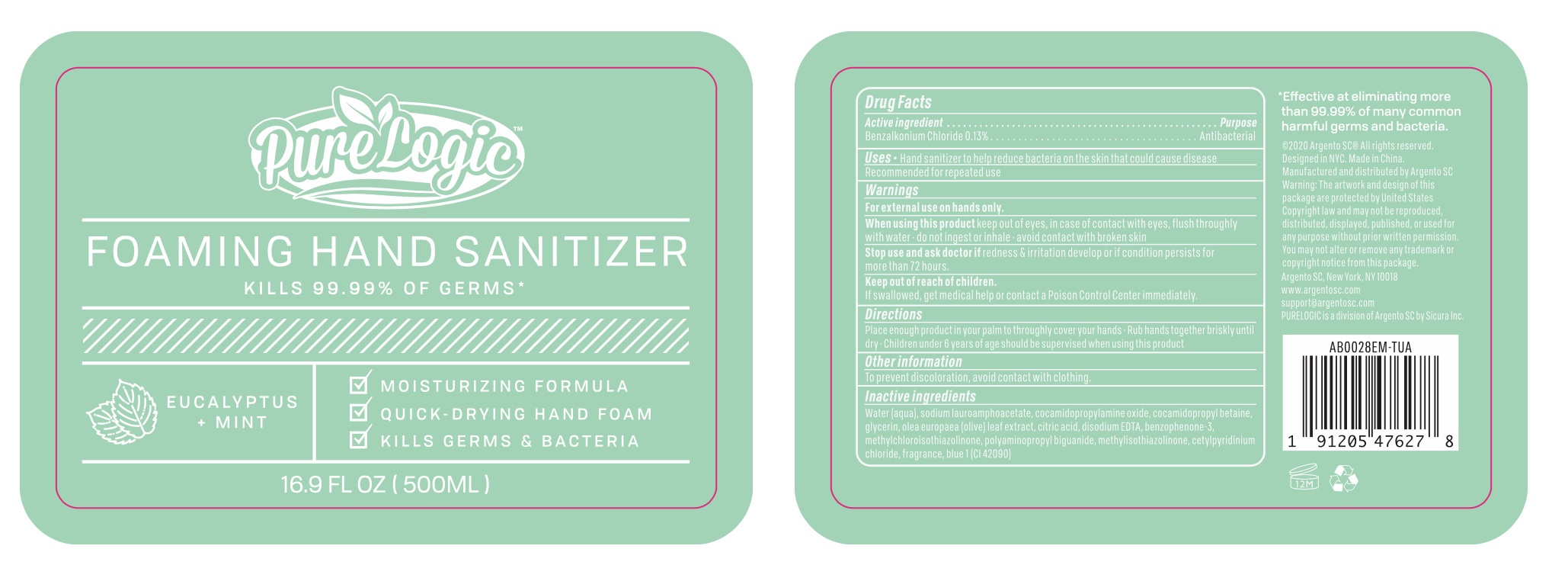 DRUG LABEL: PureLogic Foaming Hand Sanitizer Eucalyptus Mint
NDC: 77731-056 | Form: SOLUTION
Manufacturer: Argento sc by sicura inc.
Category: otc | Type: HUMAN OTC DRUG LABEL
Date: 20200801

ACTIVE INGREDIENTS: BENZALKONIUM CHLORIDE 0.13 g/100 mL
INACTIVE INGREDIENTS: SODIUM LAUROAMPHOACETATE; COCAMIDOPROPYLAMINE OXIDE; WATER; FD&C BLUE NO. 1; COCAMIDOPROPYL BETAINE; GLYCERIN; OLEA EUROPAEA LEAF; CETYLPYRIDINIUM CHLORIDE; CITRIC ACID MONOHYDRATE; DISODIUM HEDTA; BENZOPHENONE; METHYLCHLOROISOTHIAZOLINONE; METHYLISOTHIAZOLINONE

AB0028 EM foaming

Active Ingredient(s)

Benzalkonium Chloride 0.13%

Purpose:

Antibacterial

Use

Hand sanitizer to help reduce bacteria on skin that could cause disease

Recommended for repeated use

Warnings

For external use on hands only.

When using this product, keep out of eyes. In case of contact with eyes, flush thoroughly with water

Do not ingest or inhale

Avoid contact with broken skin

Stop use and ask a doctor

if irrigation and redness develop or if condition persists for more than 72 hours

Keep out of reach of children

if swallowed, get medical help or contact a Poison Control Center immediately

Directions

- Place enough product in your palm to thoroughly cover your hands. Rub hands together briskly until dry
- Children under 6 years of age should be supervised when using this product

Other information

To prevent discoloration, avoid contact with clothing

Inactive ingredients

Water, Sodium lauroamphoacetate, Cocamidopropylamine oxide, Cocamidopropyl betaine, Glycerin, Olea europaea (olive) leaf extract, Polyminopropyl biguanide, Citric acid, Disodium EDTA, Benzophenone-3, Methylchloroisothiazolinone, Methylisothiazolinone, Fragrance, Cetylpyridinium chloride, Blue 1 (CI42090)